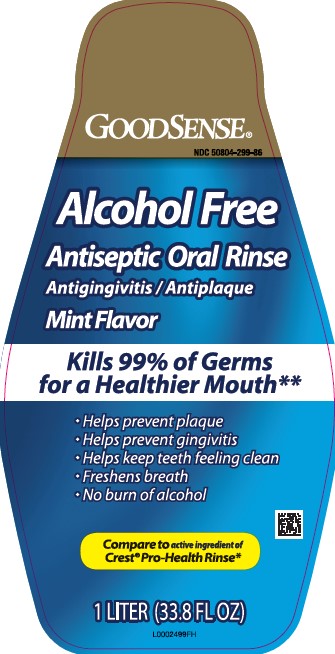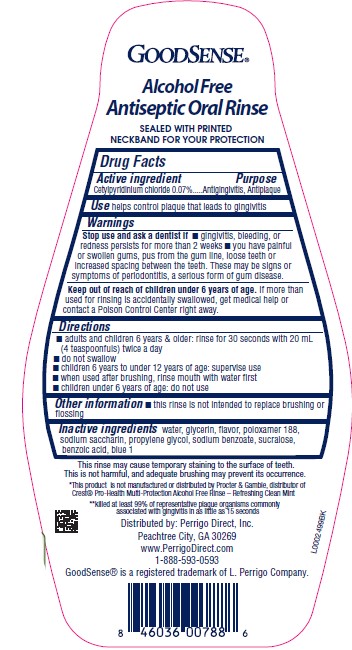 DRUG LABEL: Antiseptic
NDC: 50804-299 | Form: RINSE
Manufacturer: Perrigo Direct, Inc
Category: otc | Type: HUMAN OTC DRUG LABEL
Date: 20260219

ACTIVE INGREDIENTS: CETYLPYRIDINIUM CHLORIDE 0.7 mg/1 mL
INACTIVE INGREDIENTS: WATER; GLYCERIN; POLOXAMER 188; SACCHARIN SODIUM; PROPYLENE GLYCOL; SODIUM BENZOATE; SUCRALOSE; BENZOIC ACID; FD&C BLUE NO. 1

Good Sense 299.005/299AK-AL
Multi Action Alcohol Free Antiseptic Rinse w/CPC

claims

GOODSENSE®
Alcohol Free Antiseptic Oral Rinse

SEALED WITH PRINTED NECKBAND FOR YOUR PROTECTION

Active ingredient

Cetylpyridinium chloride 0.07%

Purpose

Antigingivitis, Antiplaque

Use

helps control plaque that leads to gingivitis

Warnings

for this product

Stop use and ask a dentist if

- gingivitis, bleeding or redness persists for more than 2 weeks
- you have painful or swollen gums, pus from the gun line, loose teeth or increased spacing between the teeth. These may be signs or symptoms of periodontitis, a serious form of gum disease.

Keep out of reach of children under 6 years of age.

If more than used for rinsing is accidentally swallowed, get medical help or contact a Poison Control Center right away.

Directions

- adults and children 6 years & older: rinse for 30 seconds with 20 mL (4 teaspoonfuls) twice a day
- do not swallow
- children 6 years to under 12 years of age: supervise use
- when used after brushing, rinse mouth with water first
- children under 6 years of age: do not use

Other information

- this rinse is not intended to replace brushing or flossing

Inactive ingredients

water, glycerin, flavor, poloxamer 188, sodium saccharin, propylene glycol, sodium benzoate, sucralose, benzoic acid, blue 1

Disclaimers

This rinse may cause temporary staining to the surface of teeth.

This is not harmful, and adequate brushing may prevent its occurrence.

*This product is not manufactured or distributed by Procter & Gamble, distributor of Crest®Pro-Health Multi-Protection Alcohol Free Rinse-Refreshing Clean Mint

**Killed at least 99% of representative plaque organisms commonly associated with gingivitis in as little as 15 seconds

ADVERSE REACTION

Distributed by: Perrigo Direct, Inc.

Peachtree City, GA 30269

www.PerrigoDirect.com

1-888-593-0593

GoodSenseis a registered trademark of L. Perrigo Company.

principal display panel

GOODSENSE®

NDC 50804-299-86

Alcohol Free

Antiseptic Oral Rinse

Antigingivitis/Antiplaque

Mint Flavor

Kills 99% of Germs for a healthier Mouth**

- Helps prevent Plaque
- Helps prevent gingivitis
- Helps keep teeth feeling clean
- Freshens Breath
- No burn of alcohol

Compare to active ingredients of Crest®Pro-Health Rinse*

1 LITER (33.8 FL OZ)